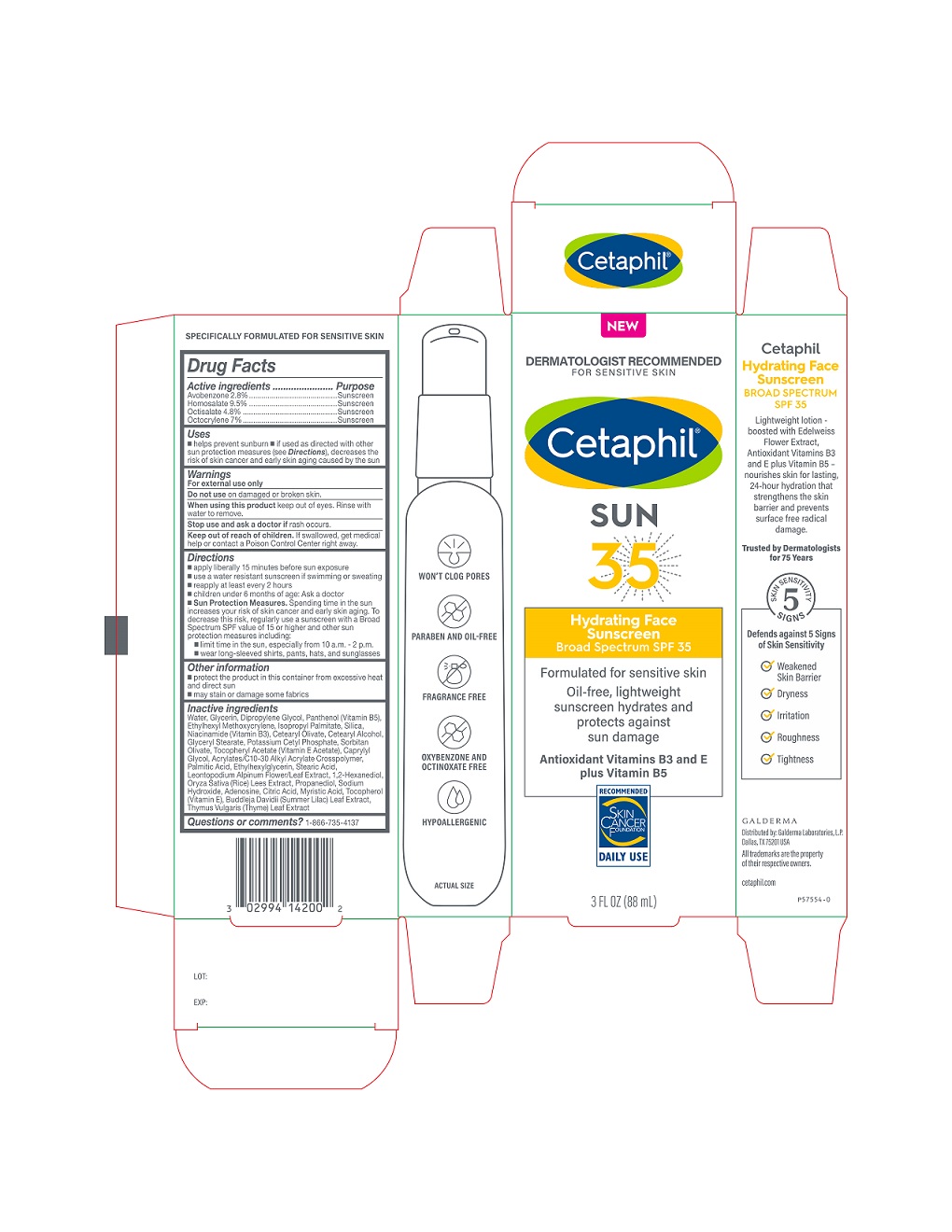 DRUG LABEL: Cetaphil Hydrating Face Sunscreen SPF 35
NDC: 0299-4142 | Form: LOTION
Manufacturer: Galderma Laboratories, L.P.
Category: otc | Type: HUMAN OTC DRUG LABEL
Date: 20231024

ACTIVE INGREDIENTS: Avobenzone 28 mg/1 mL; Homosalate 95 mg/1 mL; Octisalate 48 mg/1 mL; Octocrylene 70 mg/1 mL
INACTIVE INGREDIENTS: Water; Glycerin; Dipropylene Glycol; Panthenol; Ethylhexyl Methoxycrylene; Isopropyl Palmitate; Silicon Dioxide; Niacinamide; Cetearyl Olivate; Cetostearyl Alcohol; Glyceryl Monostearate; Potassium Cetyl Phosphate; Sorbitan Olivate; .Alpha.-Tocopherol Acetate; Caprylyl Glycol; Carbomer Interpolymer Type A (Allyl Sucrose Crosslinked); Palmitic Acid; Ethylhexylglycerin; Stearic Acid; Leontopodium Nivale Subsp. Alpinum Flowering Top; 1,2-Hexanediol; Rice Germ; Propanediol; Sodium Hydroxide; Adenosine; Citric Acid Monohydrate; Myristic Acid; Tocopherol; Buddleja Davidii Leaf; Thymus Vulgaris Leaf

Drug Fact

Active Ingredients

Avobenzone 2.8% .................Sunscreen
Homosalate 9.5% .....................Sunscreen
Octisalate 4.8% ..................Sunscreen
Octocrylene 7% .................Sunscreen

OTC - PURPOSE SECTION

Sunscreen

Uses

- helps prevent sunburn
- if used as directed with other sun protection measures (see Directions), decreases the risk of skin cancer and early skin aging caused by the sun

Warnings

For external use only

Do not use

on damaged or broken skin

When using this product

keep out of eyes. Rinse with water to remove.

Stop use and ask a doctor if

rash occurs.

Keep out of reach of children.

If swallowed, get medical help or contact a Poison Control Center right away.

Directions

- apply liberally 15 minutes before sun exposure
- use a water resistant sunscreen if swimming or sweating
- reapply at least every 2 hours
- children under 6 months of age: Ask a doctor
- Sun Protection Measures. Spending time in the sun increases your risk of skin cancer and early skin aging. To decrease this risk, regularly use a sunscreen with a Broad Spectrum SPF value of 15 or higher and other sun protection measures including:
  - limit time in the sun, especially from 10 a.m. - 2 p.m.
  - wear long-sleeved shirts, pants, hats, and sunglasses

Other information

- protect the product in this container from excessive heat and direct sun
- may stain or damage some fabrics

Inactive Ingredients

Water, Glycerin, Dipropylene Glycol, Panthenol (Vitamin B5), Ethylhexyl Methoxycrylene, lsopropyl Palmitate, Silica, Niacinamide, Cetearyl Olivate, Cetearyl Alcohol, Glyceryl Stearate, Potassium Cetyl Phosphate, Sorbitan Olivate, Tocopheryl Acetate (Vitamin E Acetate), Caprylyl Glycol, Acrylates/C10-30 Alkyl Acrylate Crosspolymer, Palmitic Acid, Ethylhexylglycerin, Stearic Acid, Leontopodium Alpinum Flower/Leaf Extract, 1,2-Hexanediol, Oryza Saliva (Rice) Lees Extract, Propanediol, Sodium Hydroxide, Adenosine, Citric Acid, Myristic Acid, Tocopherol (Vitamin E), Buddleja Davidii (Summer Lilac) Leaf Extract, Thymus Vulgaris (Thyme) Leaf Extract

Questions or comments?

1-866-735-4137

Principal Display Panel - 3 FL OZ Carton

NEW
DERMATOLOGIST RECOMMENDED
FOR SENSITIVE SKIN
Cetaphil®
SUN
35

Hydrating Face
Sunscreen
Broad Spectrum SPF 35

Formulated for sensitive skin

Oil-free, lightweight
sunscreen hydrates and
protects against
sun damage

Antioxidant Vitamins B3 and E
plus Vitamin B5

Skin Cancer Foundation logo

3 FL OZ (88 mL)
Distributed by:
Galderma Laboratories, L.P.
Dallas, Texas 75201 USA
All trademarks are the property of their respective owners.
cetaphil.com
P57554-0